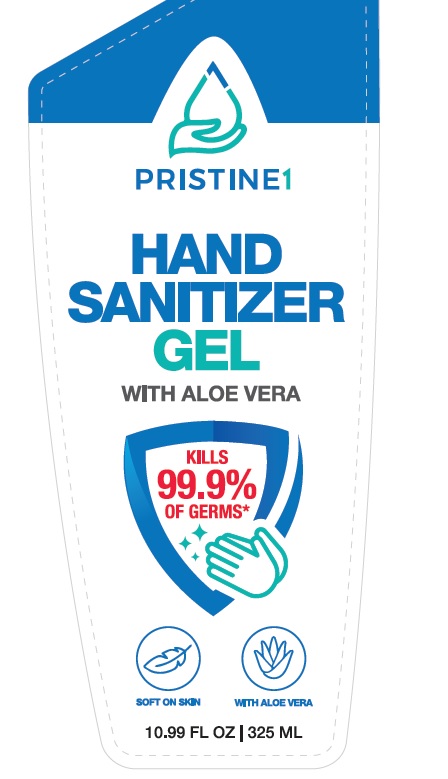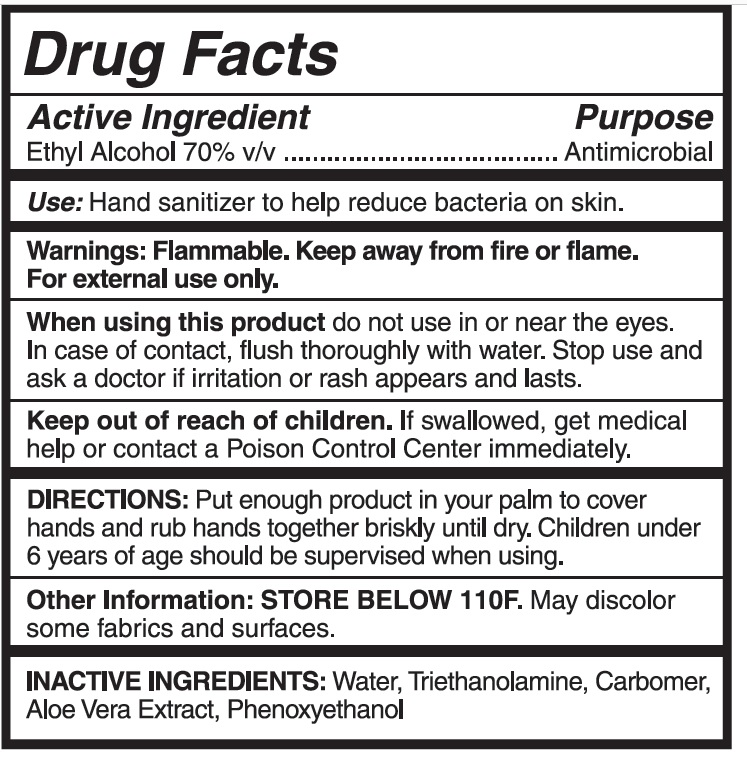 DRUG LABEL: PRISTINE1
NDC: 77605-110 | Form: GEL
Manufacturer: Caribbean Spirit Imports LLC
Category: otc | Type: HUMAN OTC DRUG LABEL
Date: 20200601

ACTIVE INGREDIENTS: ALCOHOL 0.7 mL/1 mL
INACTIVE INGREDIENTS: TROLAMINE 0.055 mL/1 mL; CARBOMER HOMOPOLYMER, UNSPECIFIED TYPE 0.002 mL/1 mL; WATER 0.45 mL/1 mL; PHENOXYETHANOL 0.006 mL/1 mL; ALOE VERA LEAF 0.001 mL/1 mL

Active Ingredient(s)

Alcohol 70% v/v. Purpose: Antimicrobial

Purpose

Antimicrobial , Hand Sanitizer

Use

Hand Sanitizer to help reduce bacteria on skin

Warnings

For external use only. Flammable. Keep away from heat or flame

Do not use

When using this product do not use in or near the eyes. In case of contact, flush thoroughly with water. Stop use and ask a doctor if irritation or rash appears and lasts.

When using this product do not use in or near the eyes. In case of contact, flush thoroughly with water. Stop use and ask a doctor if irritation or rash appears and lasts.

When using this product do not use in or near the eyes. In case of contact, flush thoroughly with water. Stop use and ask a doctor if irritation or rash appears and lasts.

Keep out of reach of children. If swallowed, get medical help or contact a Poison Control Center right away.

Directions

- Put enough product in your palm to cover hands and rub hands together briskly until dry. Children under 6 years of age should be supervised when using.

Other information

- STORE BELOW 110F. May discolor sorne fabrics and surfaces.

Inactive ingredients

Water, triethanolamine, Carbomer, Aloe vera extract, phenoxyethanol

Package Label - Principal Display Panel

Hand Sanitizer Gel with Aloe Vera

Kills 99.9% of Germs